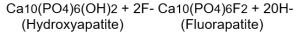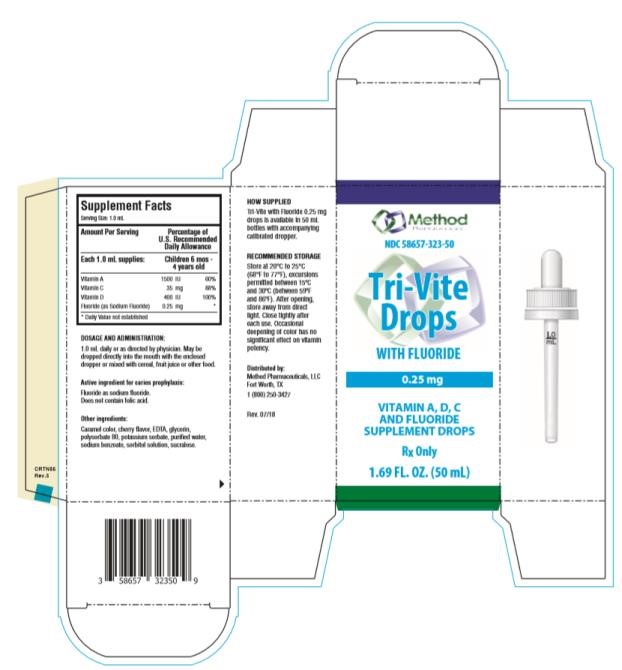 DRUG LABEL: Tri-Vite Drops with Fluoride
NDC: 58657-323 | Form: SOLUTION
Manufacturer: Method Pharmaceuticals, LLC
Category: prescription | Type: HUMAN PRESCRIPTION DRUG LABEL
Date: 20251021

ACTIVE INGREDIENTS: VITAMIN A 1500 [iU]/1 mL; ASCORBIC ACID 35 mg/1 mL; VITAMIN D 400 [iU]/1 mL; SODIUM FLUORIDE 0.25 mg/1 mL
INACTIVE INGREDIENTS: EDETIC ACID; GLYCERIN; POLYSORBATE 80; POTASSIUM SORBATE; WATER; SODIUM BENZOATE; SORBITOL; SUCRALOSE

Tri-Vite Drops with Fluroide 0_25 mg

Supplement Facts

Serving Size: 1.0 mL

Amount Per Serving |  | Percentage of U.S. Recommended Daily Allowance
Each 1.0 mL supplies: |  | Children 6 mos - 4 years old
Vitamin A | 1500 IU | 60%
Vitamin C | 35 mg | 88%
Vitamin D | 400 IU | 100%
Fluoride (as Sodium Fluoride) | 0.25 mg | *

* Daily Value not established

See INDICATIONS AND USAGE section for use by children 6 months to 6 years of age. This product does not contain the essential vitamin folic acid.

Active ingredient for caries prophylaxis: Fluoride as sodium fluoride. Does not contain folic acid.

Other ingredients: caramel color, cherry flavor, EDTA, glycerin, polysorbate 80, potassium sorbate, purified water, sodium benzoate, sorbitol solution, sucralose.

CLINICAL PHARMACOLOGY

It is well established that fluoridation of the water supply (1 ppm fluoride) during the period of tooth development leads to a significant decrease in the incidence of dental caries. Hydroxyapatite is the principal crystal for all calcified tissue in the human body. The fluoride ion reacts with hydroxyapatite in the tooth as it is formed to produce the more caries-resistant crystal, fluorapatite.

The reaction may be expressed by the equation:

Three stages of fluoride deposition in tooth enamel can be distinguished:

1. Small amounts (reflecting the low levels of fluoride in tissue fluids) are incorporated into the enamel crystals while they are being formed.

2. After enamel has been laid down, fluoride deposition continues in the surface enamel. Diffusion of fluoride from the surface inward is apparently restricted.

3. After eruption, the surface enamel acquires fluoride from water, food, supplementary fluoride and smaller amounts from saliva.

INDICATIONS AND USAGE

Supplementation of the diet with vitamins A, C and D. Tri-Vite Drops with Fluoride 0.25 mg also provides fluoride for caries prophylaxis.

The American Academy of Pediatrics recommends that children up to age 16, in areas where drinking water contains less than optimal levels of fluoride, receive daily fluoride supplementation. The American Academy of Pediatrics recommend that infants and young children 6 months to 3 years of age, in areas where the drinking water contains less than 0.3 ppm of fluoride, and children 3-6 years of age, in areas where the drinking water contains 0.3 through 0.6 ppm of fluoride, receive 0.25 mg of supplemental fluoride daily which is provided in a dose of 1 mL of Tri-Vite Drops with Fluoride 0.25 mg (See Dosage and Administration).

Tri-Vite Drops with Fluoride 0.25 mg supply significant amounts of vitamins A, C and D to supplement the diet, and to help assure that nutritional deficiencies of these vitamins will not develop. Thus, in a single easy-to-use preparation, children obtain essential vitamins and fluoride.

WARNINGS

As in the case of all medications, keep out of reach of children.

PRECAUTIONS

The suggested dose should not be exceeded since dental fluorosis may result from continued ingestion of large amounts of fluoride.

When prescribing vitamin fluoride products:

1. Determine the fluoride content of the drinking water.

2. Make sure the child is not receiving significant amounts of fluoride from other medications and swallowed toothpaste.

3. Periodically check to make sure that the child does not develop significant dental fluorosis.

Tri-Vite Drops with Fluoride 0.25 mg should be dispensed in the original plastic container, since contact with glass leads to instability and precipitation. (The amount of sodium fluoride in the 50 mL size is well below the maximum to be dispensed at one time according to recommendations of the American Dental Association.)

Important Considerations When Using Dosage Schedule:

• If fluoride level is unknown, drinking water should be tested for fluoride content before supplements are prescribed. For testing of fluoride content, contact the local or state health department.

• All sources of fluoride should be evaluated with a thorough fluoride history. Patient exposure to multiple water sources can make proper prescribing complex.

• Ingestion of higher than recommended levels of fluoride by children has been associated with an increase in mild dental fluorosis in developing, unerupted teeth.

• Fluoride supplements require long-term compliance on a daily basis.

ADVERSE REACTIONS

Allergic rash and other idiosyncrasies have been rarely reported.

DOSAGE AND ADMINISTRATION

1.0 mL daily or as directed by physician. May be dropped directly into the mouth with dropper; or mixed with cereal, fruit juice or other food.

Tri-Vite Drops with Fluoride 0.25 mg is available in 50 mL bottles with accompanying calibrated dropper.

RECOMMENDED STORAGE

Store at 20°C to 25°C (68°F to 77°F), excursions permitted between 15°C and 30°C (between 59°F and 86°F). After opening, store away from direct light. Close tightly after each use. Occasional deepening of color has no significant effect on vitamin potency.

REFRIGERATION IS NOT REQUIRED.
SHAKE WELL.

REFERENCES

1. Brudevoid F, McCann HG: Fluoride and caries control - Mechanism of action, in Nizel AE (ed): The Science of Nutrition and its Application in Clinical Dentistry. Philadelphia, WB Saunders Co, 1966, pp 331-347.

2. American Academy of Pediatrics Committee on Nutrition: Fluoride supplementation, Pediatrics 1986; 77:758.

3. American Dental Association Council on Dental Therapeutics: Accepted Dental Therapeutics, ed 38, Chicago, 1979, p321.

4. Hennon DK, Stookey GK, Muhler JC: The clinical anticariogenic effectiveness of supplementary fluoride-vitamin preparations - Results at the end of three years. J Dent Children 1966; 33 January: 3-12.

5. Hennon DK, Stookey GK, Muhler JC: The clinical anticariogenic effectiveness of supplementary fluoride-vitamin preparations - Results at the end of four years. J Dent Children 1967; 34 November; 439- 443.

6. Hennon DK, Stookey GK, Muhler JC: The clinical anticariogenic effectiveness of supplementary fluoride-vitamin preparations - Results at the end of five and a half years. Phar and Ther in Dent 1970; 1:1.

7. Hennon DK, Stookey GK, Beiswanger BB: Fluoride-vitamin supplements: Effects on dental caries and fluorosis when used in areas with suboptimum fluoride in the water supply. J Am Dent Assoc 1977; 95-965

Distributed by:
Method Pharmaceuticals, LLC
Fort Worth, TX 76118
1-877-250-3427
Rev. 07/2018

PRINCIPAL DISPLAY PANEL

NDC 58657-323-50
Tri-Vite
Drops
WITH FLUROIDE
0.25 mg
1.69 FL. OZ. (50 mL)